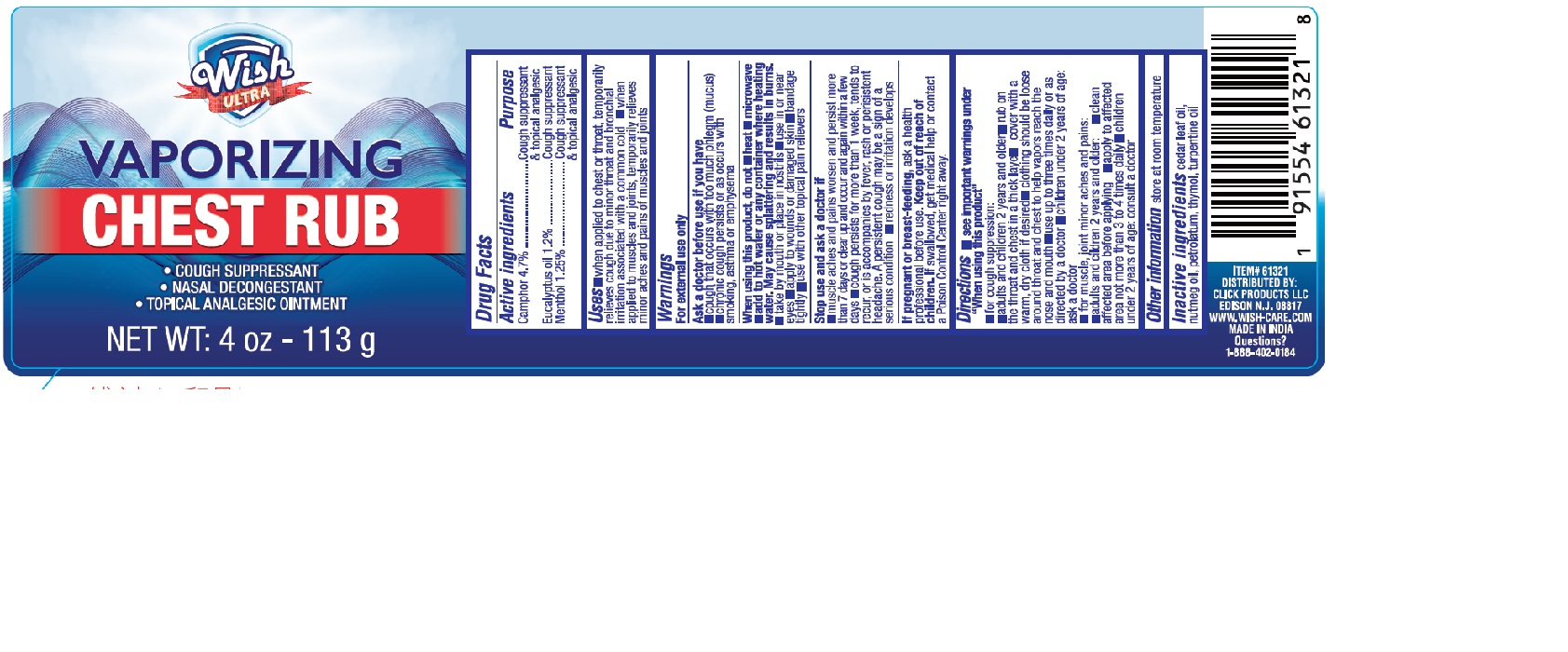 DRUG LABEL: Vaporizing chest rub
NDC: 84809-007 | Form: OINTMENT
Manufacturer: LJ Pharma
Category: otc | Type: HUMAN OTC DRUG LABEL
Date: 20250801

ACTIVE INGREDIENTS: CAMPHOR (NATURAL) 4.7 g/100 g; EUCALYPTUS OIL 1.2 g/100 g; MENTHOL, UNSPECIFIED FORM 1.25 g/100 g
INACTIVE INGREDIENTS: CEDAR LEAF OIL; NUTMEG OIL; PETROLATUM; THYMOL; TURPENTINE OIL

Active Ingredient Purpose

Camphor 4.7% Cough suppressant & topical analgesic

Eucalyptus oil 1.2% Cough suppressant

Menthol 1.25% Cough suppressant & topical analgesic

Uses

When applied to chest or throat: Temporarily relieves cough due to minor throat and bronchial irritation associated with a common cold

When applied to muscles and joints: Temporarily relieves minor aches and pains of muscles and joints

Warnings

For external use only

Ask a doctor before use if you have:

- A cough with too much phlegm (mucus)
- Chronic cough that lasts or occurs with smoking, asthma, or emphysema

When using this product, do not

:

- Heat
- Microwave
- Add to hot water or any container where heating water may cause splattering and burns
- Take by mouth or place in nostrils Use in or near eyes
- Apply to wounds or damaged skin
- Bandage tightly
- Use with other topical pain relievers

Stop Use and Ask a Doctor If

- Muscle aches and pains worsen or last more than 7 days Symptoms clear up and then return within a few days
- Cough persists more than 1 week, tends to recur, or is accompanied by: Fever, Rash, Persistent headache A persistent cough may be a sign of a serious condition
- Redness or irritation develops

If Pregnant or Breast-feeding: Ask a health professional before use.

Keep Out of Reach of Children.If swallowed, get medical help or contact a Poison Control Center right away.

Directions

See important warnings under "When using this product" For Cough Suppression:

Adults and children 2 years and older:

▪ Rub on the throat and chest in a thick layer

▪ Cover with a warm, dry cloth if desired

▪ Clothing should be loose around throat and chest to help vapors reach the nose and mouth

▪ Use up to 3 times daily or as directed by a doctor

Children under 2 years of age:

▪ Ask a doctor

For Muscle & Joint Minor Aches and Pains:

Adults and children 2 years and older:

▪ Clean affected area before applying

▪ Apply to affected area no more than 3 to 4 times daily

Children under 2 years of age:

▪ Consult a doctor

Other information

- Store at room temperature

Inactive Ingredients

Cedar leaf oil, nutmeg oil, petrolatum, thymol, turpentine oil